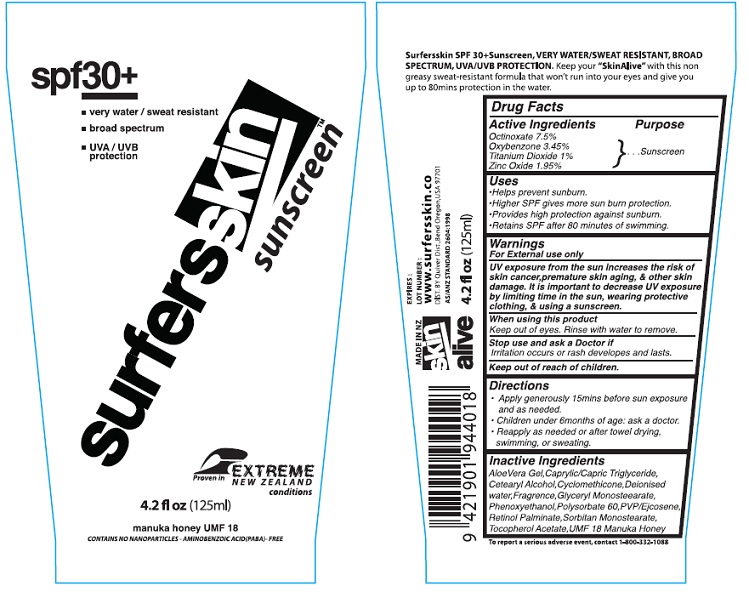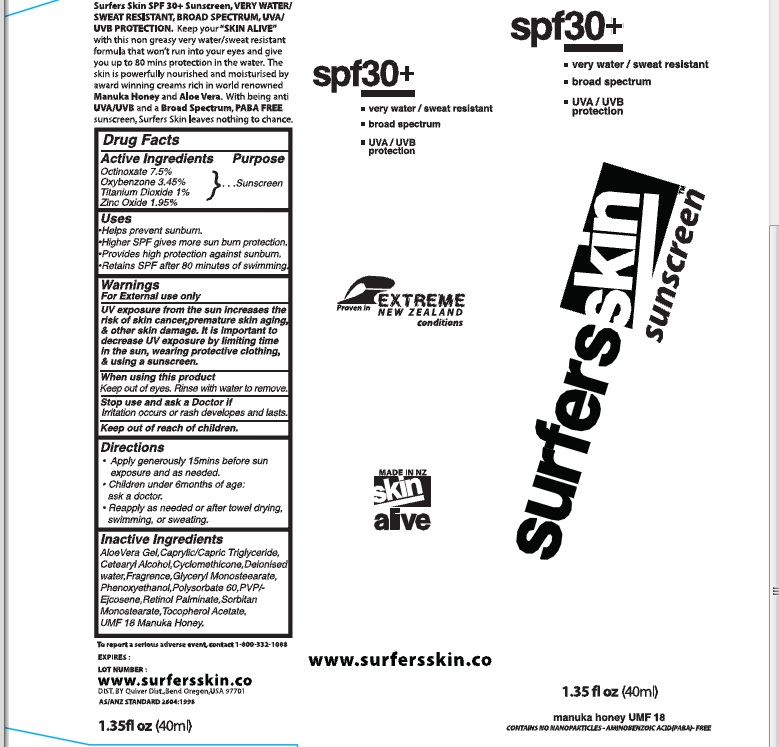 DRUG LABEL: Surfers Skin Sunscreen
NDC: 75916-4019 | Form: CREAM
Manufacturer: Skin Alive, Ltd.
Category: otc | Type: HUMAN OTC DRUG LABEL
Date: 20110131

ACTIVE INGREDIENTS: OCTINOXATE 7.5 mL/100 mL; OXYBENZONE 3.45 mL/100 mL; TITANIUM DIOXIDE 1 mL/100 mL; ZINC OXIDE 1.95 mL/100 mL
INACTIVE INGREDIENTS: ALOE VERA LEAF; MEDIUM-CHAIN TRIGLYCERIDES; CETOSTEARYL ALCOHOL; CYCLOMETHICONE; WATER; GLYCERYL MONOSTEARATE; PHENOXYETHANOL; POLYSORBATE 60; VITAMIN A PALMITATE; SORBITAN MONOSTEARATE; ALPHA-TOCOPHEROL ACETATE; HONEY

Surfers Skin Sunscreen

Active Ingredients

Octinoxate 7.5%

Oxybenzone 3.45%

Titanium Dioxide 1%

Zinc Oxide 1.95%

Purpose

Sunscreen

Uses

Helps prevent Sunburn

Higher SPF gives more sunburn protection

Provides high protection against sunburn

Retains SPF after 80 minutes of swimming

Warnings

For external use only

UV exposure from the sun increases the risk of skin cancer, premature aging and other skin damage. It is important to decrease UV exposure by limiting time in the sun, wearing protective clothing and using a sunscreen.

When using this product

Keep out of eyes. Rinse with water to remove.

Stop use and ask a doctor if

Irritation occurs or rash develops and lasts

Keep out of reach of children

Directions

Apply generously 15 min before sun exposure and as needed.

Children under 6 months of age: ask a doctor.

Reapply as needed or after towel drying, swimming, or sweating

Inactive Ingredients

Aloe Vera Gel, Caprylic/Capric Triglyceride, Cetearyl Alcohol, Cyclomethicone, Deionised Water, Fragrance, Glyceryl Monostearate, Phenoxyethanol, Polysorbate 60, PVP?ejcosene, Retinol Palminate, Sorbitan Monostearate, Tocopherol Acetate, UMF 18 Manuka Honey

DESCRIPTION

Surfersskin SPF 30+ Sunscreen, VERY WATER/SWEAT RESISTANT, BROAD SPECTRUM, UVA/UVB PROTECTION. keep your "Skin Alive" with this non greasy sweat resistant formula that won't runinto your eyes and give you up to 80 mins protection in the water.

Made in NZ

Skin alive

Expires:
Lot Number

www.surfersskin.co

DIST. BY: Quiver Dist., Bend Oregon, USA 97701

AS/ANZ STANDARD 2604-1998

4.2 fl oz (125ml)

To report a serious adverse event, contact 1-800-332-1088

PACKAGE LABEL

spf 30+

very water/sweat resistant

broad spectrum

UVA/UVB Protection

Surfersskin Sunscreen

Proven in Extreme New Zealand conditions

4.2 fl oz (125ml)

manuka honey UMF 18

CONTAINS NO NANOPARTICLES - AMINOBENZOIC ACID (PABA)-FREE